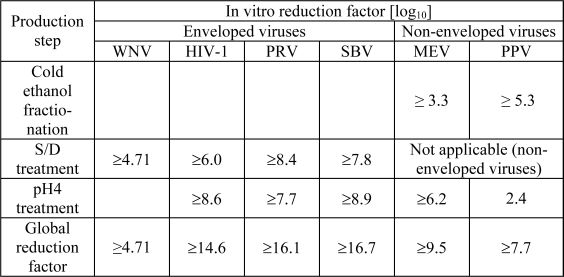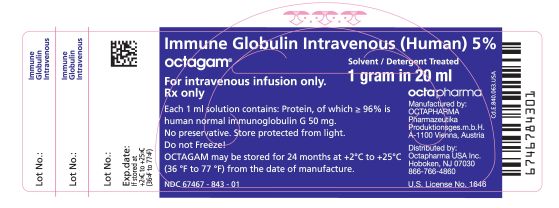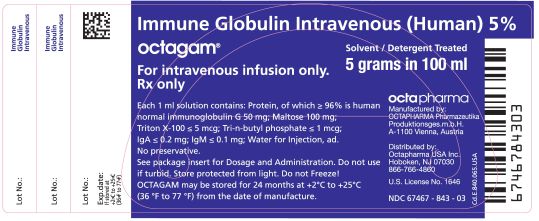 DRUG LABEL: Octagam Immune Globulin (Human)
NDC: 67467-843 | Form: SOLUTION
Manufacturer: Octapharma Pharmazeutika Produktionsgesellschaft m.b.H.
Category: prescription | Type: HUMAN PRESCRIPTION DRUG LABEL
Date: 20090909

ACTIVE INGREDIENTS: HUMAN IMMUNOGLOBULIN G 50 mg/1 mL

HIGHLIGHTS OF PRESCRIBING INFORMATION

Octagam, Immune Globulin Intravenous (Human) 5% Liquid Preparation Initial U.S. Approval: 2004 - These highlights do not include all the information needed to use Octagam, Immune Globulin Intravenous (Human), safely and effectively. See full prescribing information for Octagam.

INDICATIONS AND USAGE

Octagam is an immune globulin intravenous (human), 5% liquid, indicated for treatment of primary humoral immunodeficiency (PI) (1).

DOSAGE AND ADMINISTRATION

Intravenous use only (2).

Indication | Dose | Initial Infusion rate | Maintenance infusion rate (if tolerated)
PI | 300-600mg/kg | 0.5mg/kg/min | 3.33 mg/kg/min; Every 3-4 weeks

Ensure that patients with pre-existing renal insufficiency are not volume depleted; discontinue Octagam 5% liquid if renal function deteriorates (2.4).

For patients at risk of renal dysfunction or thrombotic events, administer Octagam 5% liquid at the minimum infusion rate practicable (2.4).

DOSAGE FORMS AND STRENGTHS

Octagam 5% liquid is supplied in 1.0 g, 2.5 g, 5 g , 10 g or 25 g single use bottles (3, 16)

CONTRAINDICATIONS

Anaphylactic or severe systemic reactions to human immunoglobulin (4)

IgA deficient patients with antibodies against IgA and a history of hypersensitivity (4)

Patients with acute hypersensitivity reaction to corn (4)

WARNINGS AND PRECAUTIONS

IgA deficient patients with antibodies against IgA are at greater risk of developing severe hypersensitivity and anaphylactic reactions Epinephrine should be available immediately to treat any acute severe hypersensitivity reactions. (5.1)

Monitor renal function, including blood urea nitrogen and serum creatinine, and urine output in patients at risk of developing acute renal failure. (5.2)

Falsely elevated blood glucose readings may occur during and after the infusion of Octagam 5% liquid with some glucometer and test strip systems (5.3)

Hyperproteinemia, increased serum viscosity and hyponatremia occur in patients receiving IGIV therapy. (5.4)

Thrombotic events have occurred in patients receiving IGIV therapy. Monitor patients with known risk factors for thrombotic events; consider baseline assessment of blood viscosity for those at risk of hyperviscosity. (5.5)

Aseptic Meningitis Syndrome has been reported with Octagam 5% liquid and other IGIV treatments, especially with high doses or rapid infusion. (5.6)

Hemolytic anemia can develop subsequent to IGIV therapy due to enhanced RBC sequestration (5.7)

IGIV recipients should be monitored for pulmonary adverse reactions (TRALI) (5.8)

The product is made from human plasma and may contain infectious agents, e.g. viruses and, theoretically, the Creutzfeldt-Jakob disease agent (5.9)

ADVERSE REACTIONS

Most common adverse reactions with an incidence of > 5% during a clinical trial were headache and nausea. (6.1). To report SUSPECTED ADVERSE REACTIONS, contact Octapharma at 1-866-766-4860 or FDA at 1-800-FDA-1088 or www.fda.gov/medwatch.

DRUG INTERACTIONS

The passive transfer of antibodies may confound the results of serological testing (7).

The passive transfer of antibodies may interfere with the response to live viral vaccines (7).

USE IN SPECIFIC POPULATIONS

Pregnancy: no human or animal data. Use only if clearly needed (8.1).

In patients over age 65 or in any person at risk of developing renal insufficiency, do not exceed the recommended dose, and infuse Octagam 5% liquid at the minimum infusion rate practicable (8.5).

See 17 for PATIENT COUNSELING INFORMATION.

Revised: September 2009

_______________________________________________________________________________________________________________________________________

FULL PRESCRIBING INFORMATION

INDICATIONS AND USAGE

Primary Humoral Immunodeficiency Diseases (PI)

Octagam is an immune globulin intravenous (human) 5% liquid indicated for treatment of primary humoral immunodeficiency (PI), such as congenital agammaglobulinemia, common variable immunodeficiency, X-linked agammaglobulinemia, Wiskott-Aldrich syndrome and severe combined immunodeficiencies.

DOSAGE AND ADMINISTRATION

For intravenously use only

Preparation and handling

- Octagam 5% liquid should be inspected visually for particulate matter and discoloration prior to administration, whenever solution and container permit. Do not use if turbid and/or discoloration is observed.
- Octagam 5% liquid must not be mixed with other medicinal products or administered simultaneously with other intravenous preparation in the same infusion set. Do not mix with immune globulin intravenous (IGIV) products from other manufacturers.
- Do not freeze. Solutions that have been frozen should not be used.
- Octagam 5% liquid bottle is for single use only. Octagam 5% liquid contains no preservative. Any bottle that has been entered should be used promptly. Partially used bottles should be discarded.
- Content of Octagam 5% liquid bottles may be pooled under aseptic conditions into sterile infusion bags and infused within 8 hours after pooling.
- Do not use after expiration date.
- Octagam 5% liquid should not be diluted.

Treatment of Primary Humoral Immunodeficiency

As there are significant differences in the half-life of IgG among patients with primary humoral immunodeficiencies, the frequency and amount of immunoglobulin therapy may vary from patient to patient. The proper amount can be determined by monitoring clinical response.

The dose of Octagam 5% liquid for replacement therapy in primary humoral immunodeficiency diseases is 300 to 600 mg/kg body weight (6-12ml/kg) administered every 3 to 4 weeks. The dosage may be adjusted over time to achieve the desired trough levels and clinical responses.

If a patient is at risk of measles exposure (ie., outbreak in US or travel to endemic areas outside of the US) and receives a dose of less than 400 mg/kg every 3 to 4 weeks, the dose should be increased to at least 400 mg/kg. If a patient has been exposed to measles, this dose should be administered as soon as possible after exposure.

Missed Doses

If a patient on regular treatment missed a dose, the missed dose should be administered as soon as possible, and then treatment should continue as before.

Administration

Octagam 5% liquid should be inspected visually for particulate matter and discoloration prior to administration, whenever solution and container permit. Do not use if turbid and/or discoloration is observed.

Octagam 5% liquid should be at room temperature during administration. Only administer intravenously.

Any bottle that has been opened should be used promptly. Partially used bottles should be discarded.

Octagam 5% liquid is not supplied with an infusion set. If an in-line filter is used the pore size should be 0.2 – 200 microns.

Do not use a needle of larger than 16 gauge to prevent the possibility of coring. Insert needle only once, within the stopper area delineated (by the raised ring for penetration). The stopper should be penetrated perpendicular to the plane of the stopper within the ring.

Rate of Administration

It is recommended that Octagam 5% liquid be initially infused at infusion rates stated below, at least until the physician has had adequate experience with a given patient.

Infusion rates: 0.5mg/kg/min (30mg/kg/hr for the first 30 minutes; if tolerated, advance to 1mg/kg/min (60mg/kg/hr) for the second 30 minutes; and if further tolerated, advance to 2mg/kg/min (120mg/kg/hr) for the third 30 minutes. Thereafter the infusion can be maintained at a rate up to, but not exceeding, 3.33mg/kg/min (200mg/kg/hr)

For patients judged to be at risk for developing renal dysfunction, administer Octagam 5% liquid at the minimum infusion rate practicable, not to exceed 0.07 ml/kg (3.3 mg/kg)/minute (200 mg/kg/hour).

Table 1

Rate of Administration | mg/kg/min (mg/kg/hour) | ml/kg/min
first 30 min | 0.5 (30) | 0.01
next 30 min | 1.0 (60) | 0.02
next 30 min | 2.0 (120) | 0.04
Maximum | < 3.33 (<200) | <0.07

Certain severe adverse drug reactions may be related to the rate of infusion. Slowing or stopping the infusion usually allows the symptoms to disappear promptly.

Ensure that patients with pre-existing renal insufficiency are not volume depleted; discontinue Octagam 5% liquid if renal function deteriorates.

For patients at risk of renal dysfunction or thromboembolic events, administer Octagam 5% liquid at the minimum infusion rate practicable.

Incompatibilities

Octagam 5% liquid must not be mixed with other medicinal products or administered simultaneously with other intravenous preparations in the same infusion set.

Shelf-life

Octagam 5% liquid may be stored for 24 months at +2°C to + 25°C (36°F to 77°F) from the date of manufacture.

Special Precautions for Storage

Do not freeze. Frozen product should not be used.

Do not use after expiration date.

DOSAGE FORMS AND STRENGTHS

Octagam 5% liquid is supplied in 1.0 g, 2.5 g, 5 g , 10 g or 25 g single use bottles (See How Supplied/Storage and Handling [16]).

CONTRAINDICATIONS

Octagam 5% liquid is contraindicated in patients who have acute severe hypersensitivity reactions to human immunoglobulin.

Octagam 5% liquid contains trace amounts of IgA (not more than 0.2 mg/ml in a 5% solution). It is contraindicated in IgA deficient patients with antibodies against IgA and history of hypersensitivity (See Description [11]).

Octagam 5% liquid is contraindicated in patients with acute hypersensitivity reaction to corn. Octagam 5% liquid contains maltose, a disaccharide sugar which is derived from corn. Patients known to have corn allergies should avoid using Octagam 5% liquid.

WARNINGS AND PRECAUTIONS

Sensitivity

Severe hypersensitivity reactions may occur [ 1 ] (See Contraindications [4.1]). In case of hypersensitivity, Octagam 5% liquid infusion should be immediately discontinued and appropriate treatment instituted. Epinephrine should be immediately available for treatment of acute severe hypersensitivity reaction. IgA deficient patients with antibodies against IgA are at greater risk of developing severe hypersensitivity and anaphylactoid reactions when administered Octagam 5% liquid (See Contraindications [4.2]). Patients known to have corn allergies should avoid using Octagam 5% liquid (See Contraindications [4.3]).

Renal Failure

Assure that patients are not volume depleted prior to the initiation of the infusion of Octagam 5% liquid.

Periodic monitoring of renal function tests and urine output is particularly important in patients judged to have a potential increased risk of developing acute renal failure. Renal function, including a measurement of blood urea nitrogen (BUN)/serum creatinine, should be assessed prior to the initial infusion of Octagam 5% liquid and again at appropriate intervals thereafter. If renal function deteriorates, discontinuation of the product should be considered (See Patient Counselling Information [17])

For patients judged to be at risk for developing renal dysfunction and/or at risk of developing thrombotic events, it may be prudent to reduce the amount of product infused per unit time by infusing Octagam 5% liquid at a maximum rate less than 0.07 ml/kg (3.3 mg/kg)/minute (200 mg/kg/hour) (See Boxed Warning, and Dosage and Administration [2.4]).

Blood Glucose Monitoring

Blood Glucose Testing [ 2 ] :some types of blood glucose testing systems (for example, those based on the glucose dehydrogenase pyrroloquinolinequinone (GDH-PQQ) or glucose-dye-oxidoreductase methods) falsely interpret the maltose contained in Octagam 5% liquid as glucose. This has resulted in falsely elevated glucose readings and, consequently, in the inappropriate administration of insulin, resulting in life-threatening hypoglycemia. Also, cases of true hypoglycemia may go untreated if the hypoglycemic state is masked by falsely elevated glucose readings. Accordingly, when administering Octagam 5% liquid, the measurement of blood glucose must be done with a glucose-specific method. The product information of the blood glucose testing system, including that of the test strips, should be carefully reviewed to determine if the system is appropriate for use with maltose-containing parenteral products. If any uncertainty exists, contact the manufacturer of the testing system to determine if the system is appropriate for use with maltose-containing parenteral products.

Hyperproteinemia

Hyperproteinemia, increased serum viscosity and hyponatremia may occur in patients receiving IGIV therapy. The hyponatremia is likely to be a pseudohyponatremia as demonstrated by a decreased calculated serum osmolality or elevated osmolar gap. Distinguishing true hyponatremia from pseudohyponatremia is clinically critical, as treatment aimed at decreasing serum free water in patients with pseudohyponatremia may lead to volume depletion, a further increase in serum viscosity and a disposition to thromboembolic events [ 3 ].

Thrombotic events

Thrombotic events have been reported in association with IGIV therapy [ 4 ],[ 5 ],[ 6 ]. Patients at risk may include those with a history of atherosclerosis, multiple cardiovascular risk factors, advanced age, impaired cardiac output, coagulation disorders, prolonged periods of immobilization and/or known or suspected hyperviscosity. The potential risks and benefits of IGIV should be weighed against those of alternative therapies for all patients for whom IGIV administration is being considered. Baseline assessment of blood viscosity should be considered in patients at risk for hyperviscosity, including those with cryoglobulins, fasting chylomicronemia / markedly high triacylglycerols (triglycerides), or monoclonal gammopathies.

Aseptic meningitis syndrome (AMS) has been reported to occur infrequently in association with IGIV treatment. Discontinuation of IGIV treatment has resulted in remission of AMS within several days without sequelae. The syndrome usually begins within several hours to two days following IGIV treatment and rapid infusion. It is characterized by symptoms and signs including severe headache, nuchal rigidity, drowsiness, fever, photophobia, painful eye movements, nausea and vomiting. Cerebrospinal fluid (CSF) studies are frequently positive with pleocytosis up to several thousand cells per cu mm, predominantly from the granulocytic series, and elevated protein levels up to several hundred mg/dl. Patients exhibiting such symptoms and signs should receive a thorough neurological examination, including CSF studies, to rule out other causes of meningitis. It appears that patients with a history of migraine may be more susceptible. [ 7 ] (See Patient Counselling Information [17]).

Hemolysis

IGIV products can contain blood group antibodies which may act as hemolysins and induce in vivo coating of red blood cells with immunoglobulin, causing a positive direct antiglobulin reaction and, rarely, hemolysis [ 8 ]. Hemolytic anemia can develop subsequent to IGIV therapy due to enhanced RBC sequestration [See ADVERSE REACTIONS] [ 9 ]. IGIV recipients should be monitored for clinical signs and symptoms of hemolysis. If signs and/or symptoms of hemolysis are present after IGIV infusion, appropriate confirmatory laboratory testing should be done (See Patient Counseling Information [17]).

Transfusion-Related Acute Lung Injury (TRALI)

There have been reports of noncardiogenic pulmonary edema [Transfusion-Related Acute Lung Injury (TRALI)] in patients administered IGIV [ 10 ]. TRALI is characterized by severe respiratory distress, pulmonary edema, hypoxemia, normal left ventricular function, and fever and typically occurs within 1-6 hours after transfusion. Patients with TRALI may be managed using oxygen therapy with adequate ventilatory support.

IGIV recipients should be monitored for pulmonary adverse reactions (See Patient Counseling Information [17]). If TRALI is suspected, appropriate tests should be performed for the presence of anti-neutrophil antibodies in both the product and patient serum.

General

Because this product is made from human blood, it may carry a risk of transmitting infectious agents, e.g., viruses and theoretically, the Creutzfeldt-Jakob disease (CJD) agent. All infections thought by a physician possibly to have been transmitted by this product should be reported by the physician or other healthcare provider to Octapharma. The physician should discuss the risks and benefits of this product with the patient, before prescribing or administering it to the patient (See Patient Counseling Information [17]).

Laboratory Tests

If signs and/or symptoms of hemolysis are present after IGIV infusion, appropriate confirmatory laboratory testing should be done.

If TRALI is susppected, appropriate tests should be performed for the presence of anti-neutrophil antibodies in both the product and patient serum.

Because of the potentially increased risk of thrombosis, baseline assessment of blood viscosity should be considered in patients at risk for hyperviscosity, including those with cryoglobulins, fasting chylomicronemia/markedly high triacylglycerols (triglycerides), or monoclonal gammopathies.

ADVERSE REACTIONS

Adverse Drug Reaction Overview

The most serious adverse reactions observed with Octagam 5% Liquid treatment have been immediate anaphylactic reactions, aseptic meningitis, and hemolytic anemia.

The most common adverse reactions observed with Octagam 5% Liquid treatment during clinical trial (> 5%) were headache and nausea.

Clinical Trials Experience

Because clinical trials are conducted under widely varying conditions, adverse reaction rates observed in the clinical trials of a product cannot be directly compared to rates in the clinical trials of another product and may not reflect the rates observed in clinical practice.

The clinical trial database includes a multi-center, open-label, single arm study in 46 children and adults with PI. Subjects participated in the study for a mean of 346 days and received 300 to 450 mg/kg every 21 days or 400 to 600 mg/kg every 28 days. Infusions were initiated at a rate of 30 mg/kg/hour for the first 30 minutes, and, if tolerated, could be advanced to a maximum tolerated rate not exceeding 200 mg/kg/hour. Over half of the subjects were male (n=28; 61%), and more than half were on the 28-day infusion schedule (n=27; 59%). The mean age of subjects was 31.5 years.

Six subjects experienced a total of 12 SAEs (abdominal pain (2 occurrences), cardiac arrest, pneumonia, cellulitis, coxsackie viral infection, renal calculus (2 occurrences), blood culture positive, ketonuria, gastroenteritis, and colitis pseudomembranosus). Eleven of the 12 SAEs were not suspected to be related to study drug; the other SAE was noted before the subject began receiving the next scheduled infusion, and it was not temporally related to the previous infusion.

Pre-medications were used in 165 (25.2%) out of 654 infusions and in 14 (30.4%) out of 46 patients. Infusions were slowed or interrupted in 9 out of 489 infusions (1.84%) without pre-medication and in 10 out of 165 infusions (6.06%) with pre-medication. Five out of 32 (15.63%) patients who never received any pre-medication had at least one slowed or interrupted infusion, whereas 9 out of 14 (64.29%) patients who received pre-medication at least once also had a slowed or interrupted infusion.

Six of the 46 subjects in the trial (13%) were withdrawn from the study: 2 on the subjects' request; 1 because of investigator's decision (non-compliance); 1 because of loss to follow-up; 1 death (cardiac arrest, not suspected to be related to study drug); and 1 by error of the study coordinator.

All adverse events in trial OCTA-06, irrespective of the causality assessment, reported by at least 5% of subjects during the 12-months treatment are given in the table below.

Table 2: Subjects and Infusions with at least one Adverse Event Irrespective of Causality (Study OCTA-06)

 | Octagam | 5% liquid
 | No. of subjects (%) | No. of infusions (%)
Total | 46 (100%) | 654 (100%)
Nasal congestion | 24 (52%) | 39 (6%)
Sinusitis NOS | 23 (50%) | 45 (7%)
Headache NOS | 22 (48%) | 62 (9%)
Cough | 20 (43%) | 46 (7%)
Sore throat NOS | 16 (35%) | 25 (4%)
Fever | 15 (33%) | 19 (3%)
Vomiting NOS | 12 (26%) | 15 (2%)
Diarrhoea NOS | 11 (24%) | 22 (3%)
Bronchitis NOS | 10 (22%) | 14 (2%)
Abdominal pain upper | 9 (20%) | 11 (2%)
Arthralgia | 9 (20%) | 15 (2%)
Nasopharyngitis | 8 (17%) | 14 (2%)
Rhinorrhoea | 8 (17%) | 9 (1%)
Upper respiratory tract infection NOS | 8 (17%) | 13 (2%)
Fatigue | 7 (15%) | 9 (1%)
Nausea | 7 (15%) | 8 (1%)
Pain in limb | 7 (15%) | 10 (2%)
Sinus congestion | 7 (15%) | 9 (1%)
Back pain | 5 (11%) | 10 (2%)
Injection site reaction NOS | 5 (11%) | 11 (2%)
Wheezing | 5 (11%) | 8 (1%)
Asthma NOS | 4 (9%) | 5 (0.8%)
Asthma aggravated | 4 (9%) | 10 (2%)
Chest pain NEC | 4 (9%) | 4 (0.6%)
Conjunctivitis NEC | 4 (9%) | 4 (0.6%)
Dyspepsia | 4 (9%) | 5 (0.8%)
Earache | 4 (9%) | 6 (0.9%)
Ecchymosis | 4 (9%) | 7 (1%)
Fungal infection NOS | 4 (9%) | 4 (0.6%)
Injection site pain | 4 (9%) | 4 (0.6%)
Insomnia NEC | 4 (9%) | 4 (0.6%)
Sinusitis acute NOS | 4 (9%) | 8 (1%)
Urinary tract infection NOS | 4 (9%) | 8 (1%)
Vaginal candidiasis | 4 (9%) | 7 (1%)
Abdominal pain NOS | 3 (7%) | 3 (0.5%)
Dizziness (exc vertigo) | 3 (7%) | 4 (0.6%)
Dyspnoea NOS | 3 (7%) | 3 (0.5%)
Epistaxis | 3 (7%) | 5 (0.8%)
Eye discharge | 3 (7%) | 3 (0.5%)
Eye irritation | 3 (7%) | 3 (0.5%)
Hypertension NOS | 3 (7%) | 5 (0.8%)
Otitis media NOS | 3 (7%) | 4 (0.6%)
Pain NOS | 3 (7%) | 4 (0.6%)
Postnasal drip | 3 (7%) | 3 (0.5%)
Productive cough | 3 (7%) | 3 (0.5%)
Rigors | 3 (7%) | 4 (0.6%)
Throat irritation | 3 (7%) | 3 (0.5%)
Urticaria NOS | 3 (7%) | 8 (1%)

The adverse reactions in trial OCTA-06 reported by at least 5% of subjects during the 12-month treatment are given in the table below.

Table 3: Subjects and Infusions with At Least One Adverse Reaction (Study OCTA-06)

 | Octagam | 5% liquid
 | No. of subjects (%) | No. of infusions (%)
Total | 46 (100%) | 654 (100%)
Headache NOS | 7 (15%) | 18 (3%)
Nausea | 3 (7%) | 4 (0.6%)

The following table provides an overview on the temporally associated adverse events (TAAEs) during and within different time-points after the end of Octagam infusion.

Table 4: Overview on TAAEs Occurring During and Over a Specified Number of Hours after the End of Infusion, Irrespective of Causality (Study OCTA-06)

Total # of infusions (N=654) | Time-Points
 | 24 hrs | 48hrs | 72hrs
Total # of TAAEs | 172 | 183 | 189
Proportion of infusions with TAAEs | 26.3% | 28.0% | 28.9%
Upper bound 1 sided 97.5% CI for proportion of TAAEs | 29.7% | 31.4% | 32.4%

All temporally associated adverse events (TAAEs) in trial OCTA-06, irrespective of the causality assessment, reported by at least 5% of subjects within 72 hours after the end of the infusion are given in the table below.

Table 5: TAAEs During and Over 72 Hours After End of Infusion, Irrespective of Causality (Study OCTA-06)

TAAE | Subjects (%)n=46 | Infusion (%)N=654
Headache NOS | 15 (32.6%) | 28 (4.3%)
Sinusitis NOS | 12 (26.1%) | 13 (2.0%)
Nasal congestion | 10 (21.7%) | 11 (1.7%)
Arthralgia | 7 (15.2%) | 10 (1.5%)
Cough | 7 (15.2%) | 7 (1.1%)
Injection site reaction NOS | 5 (10.9%) | 11 (1.7%)
Sore throat NOS | 5 (10.9%) | 5 (0.8%)
Vomiting NOS | 5 (10.9%) | 5 (0.8%)
Back pain | 4 (8.7%) | 6 (0.9%)
Diarrhoea NOS | 4 (8.7%) | 5 (0.8%)
Ecchymosis | 4 (8.7%) | 5 (0.8%)
Injection site pain | 4 (8.7%) | 4 (0.6%)
Nausea | 4 (8.7%) | 5 (0.8%)
Upper respiratory tract infection NOS | 4 (8.7%) | 5 (0.8%)
Wheezing | 4 (8.7%) | 6 (0.9%)
Asthma aggravated | 3 (6.5%) | 4 (0.6%)
Eye irritation | 3 (6.5%) | 3 (0.5%)
Fungal infection NOS | 3 (6.5%) | 3 (0.5%)
Pain in limb | 3 (6.5%) | 5 (0.8%)
Rhinorrhoea | 3 (6.5%) | 3 (0.5%)
Urinary tract infection NOS | 3 (6.5%) | 3 (0.5%)

The subset of drug related temporally associated adverse events (TAAEs) in trial OCTA-06 reported by at least 5% of subjects within 72 hours after the end of the infusion is given in the table below.

Table 6: Drug-Related TAAEs During and Over 72 Hours After End of Infusion (Study OCTA-06)

TAAE | Subjects (%)n=46 | Infusion (%)N=654
Headache NOS | 6 (13.0%) | 15 (2.3%)
Nausea | 3 (6.5%) | 4 (0.6%)

Laboratory Abnormalities

Standard clinical laboratory evaluations were performed Study OCTA-06. Three subjects (7%) had incidences of AST (>2.5 x ULN) which were all assessed as clinically non-significant. Four subjects (9%) had incidences of serum creatinine increases being stable throughout the course of the study. Therefore, these observations were not regarded as indicative of acute renal dysfunction.

Postmarketing Experience

Because postmarketing reporting of adverse reactions is voluntary and from a population of uncertain size, it is not always possible to reliably estimate the frequency of these reactions or establish a causal relationship to product exposure.

Octagam 5% liquid Postmarketing Experience

The following adverse reactions have been identified during post-approval use of Octagam 5% liquid. Because these reactions are reported voluntarily from a population of uncertain size, it is not always possible to reliably estimate their frequency or to establish a causal relationship to Octagam 5% liquid.

Blood and lymphatic system disordersLeukopenia, haemolytic anaemia

Immune system disorders

Hypersensitivity, anaphylactic shock, anaphylactic reaction, anaphylactoid reaction, angioneurotic oedema, face oedema

Metabolic and nutritional disorders

Fluid overload

Psychiatric disorders

Agitation

Nervous system disorders

Headache, cerebrovascular accident, meningitis aseptic, migraine, dizziness, paraesthesia

Cardiac disorders

Myocardial infarction, tachycardia, palpitations, cyanosis

Vascular disorders

Hypotension, thrombosis, peripheral circulatory failure, hypertension

Respiratory, thoracic and mediastinal disorders

Respiratory failure, pulmonary embolism, pulmonary oedema, bronchospasm, dyspnoea, cough

Gastrointestinal disorders

Nausea, vomiting, diarrhoea, abdominal pain

Skin and subcutaneous tissue disorders

Eczema, urticaria, rash, rash erythematous, dermatitis, pruritus, alopecia

Musculoskeletal and connective tissue disorders

Back pain, arthralgia, myalgia, pain in extremity

Renal and urinary disorders

Renal failure acute

General disorders and administration site conditions

Fatigue, injection site reaction, pyrexia, chills, chest pain, hot flush, flushing, hyperhidrosis, malaise

Investigations

Hepatic enzymes increased, blood glucose false positive

General

The following adverse reactions have been identified during post-approval use of IGIV products. Because these reactions are reported voluntarily from a population of uncertain size, it is not always possible to reliably estimate their frequency or to establish a causal relationship to IGIV products:

RespiratoryApnea, Acute Respiratory Distress Syndrome (ARDS), Transfusion Related Acute Lung Injury (TRALI), cyanosis, hypoxemia, pulmonary edema, dyspnea, bronchospasm

Cardiovascular

Cardiac arrest, thromboembolism, vascular collapse, hypotension

Neurological

Coma, loss of consciousness, seizures, tremor

Integumentary

Steven-Johnson syndrome, epidermolysis, erythema multiforme, bullous dermatitis

Hematologic

Pancytopenia, leukopenia, hemolysis, positive direct antiglobulin (Coombs) test

General / Body as a Whole

Pyrexia, rigors

Musculoskeletal

Back pain

Gastrointestinal

Hepatic dysfunction, abdominal pain

DRUG INTERACTIONS

Admixtures of Octagam 5% liquid with other drugs and intravenous solutions have not been evaluated. It is recommended that Octagam 5% liquid be administered separately from other drugs or medications which the patient may be receiving. The product should not be mixed with IGIVs from other manufacturers.

The infusion line may be flushed before and after administration of Octagam 5% liquid with either normal saline or 5% dextrose in water.

Various passively transferred antibodies in immunoglobulin preparations can confound the results of serological testing.

Antibodies in Octagam 5% liquid may interfere with the response to live viral vaccines, such as measles, mumps, and rubella. Physicians should be informed of recent therapy with IGIVs, so that administration of live viral vaccines, if indicated, can be appropriately delayed 3 or more months from the time of IGIV administration.

USE IN SPECIFIC POPULATIONS

Pregnancy

Pregnancy Category C. Animal reproduction studies have not been conducted with Octagam 5% liquid. It is also not known whether Octagam 5% liquid can cause fetal harm when administered to a pregnant woman or can affect reproduction capacity. Octagam 5% liquid should be given to a pregnant woman only if clearly needed.

Nursing Mothers

Octagam 5% liquid has not been evaluated in nursing mothers.

Pediatric Use

Octagam 5% liquid was evaluated in 11 pediatric subjects (age range 6 – 16 years). There were no obvious differences observed between adults and pediatric subjects with respect to pharmacokinetics, efficacy and safety. No pediatric specific dose requirements were necessary to achieve the desired serum IgG levels.

Geriatric Use

Patients > 65 years of age may be at increased risk for developing certain adverse reactions such as thromboembolic events and acute renal failure (See Boxed Warnings and Precautions [5.3]). In the clinical trial only 4 geriatric patients (> 65 years) were enrolled, a number insufficient to determine whether geriatric patients respond differently from younger subjects. In these 4 patients no particular issues were observed.

OVERDOSAGE

Overdose may lead to fluid overload and hyperviscosity, particularly in the elderly and in patients with impaired renal function.

DESCRIPTION

Immune Globulin Intravenous (Human), Octagam 5% liquid, is a solvent/detergent (S/D)-treated, sterile preparation of highly purified immunoglobulin G (IgG) derived from large pools of human plasma. Octagam 5% liquid is a solution for infusion which must be administered intravenously.

All units of human plasma used in the manufacture of Octagam 5% liquid are provided by FDA-approved blood establishments only, and are tested by FDA-licensed serological tests for HBsAg, antibodies to HCV and HIV and Nucleic Acid Test (NAT) for HCV and HIV-1 and found to be non-reactive (negative).

The product is manufactured by the cold ethanol fractionation process followed by ultrafiltration and chromatography. The manufacturing process includes treatment with an organic S/D mixture composed of tri-n-butyl phosphate (TNBP) and Triton X-100 (Octoxynol). The Octagam 5% liquid manufacturing process provides a significant viral reduction in in vitro studies (table 7). These reductions are achieved through a combination of process steps including cold ethanol fractionation, S/D treatment and pH 4 treatment.

Table 7: In vitro reduction factor during Octagam 5% liquid manufacturing

WNV: West Nile Virus

HIV-1: Human Immunodeficiency Virus - 1

PRV: Pseudorabies Virus

SBV: Sindbis Virus

MEV: Mouse Encephalomyelitis Virus

PPV: Porcine Parvovirus

Composition

The composition of Octagam 5% liquid is shown in table 8 as follows:

Table 8 : Composition

Component | Quantity/ml
Protein, of which not less than 96% is human normal immunoglobulin G | 50 mg
Maltose | 100 mg
Triton X-100 | not more than 5 mcg
TNBP | not more than 1 mcg
IgA | not more than 0.2 mg
IgM | not more than 0.1 mg
Water for Injection | ad.

This preparation contains approximately 50 mg of protein per ml (5%) of which not less than 96% is human normal immunoglobulin G. Octagam 5% liquid contains not more than 3% aggregates, not less than 90% monomers and dimers and not more than 3% fragments.

The sodium content of the final solution is not more than 30 mmol/l and the pH is between 5.1 and 6.0. The osmolality is 310 - 380 mosmol/kg.

The manufacturing process for Octagam 5% liquid isolates IgG without additional chemical or enzymatic modification, and the Fc portion is maintained intact Octagam 5% liquid contains the IgG antibody activities present in the donor population. IgG subclasses are fully represented with the following approximate percents of total IgG: IgG 1 is 65%, IgG 2 is 30%, IgG 3 is 3% and IgG 4 is 2%.

Octagam 5% liquid contains a broad spectrum of IgG antibodies against bacterial and viral agents that are capable of opsonization and neutralization of microbes and toxins.

Octagam 5% liquid contains no preservative and no sucrose.

CLINICAL PHARMACOLOGY

Mechanism of Action

Octagam 5% liquid supplies a broad spectrum of opsonic and neutralizing IgG antibodies against bacteria or their toxins. The mechanism of action in PI has not been fully elucidated.

Pharmacodynamics

Octagam 5% liquid contains mainly immunoglobulin G (IgG) with a broad spectrum of antibodies against various infectious agents reflecting the IgG activity found in the donor population. Octagam 5% liquid which is prepared from pooled material from not less than 1000 donors, has an IgG subclass distribution similar to that of native human plasma. Adequate doses of IGIV can restore abnormally low IgG level to the normal range. Standard pharmacodynamic studies were not performed.

Pharmacokinetics

Peak levels of IgG are reached immediately after infusion of Octagam 5% liquid. It has been shown that after infusion, exogenous IgG is distributed relatively rapidly between plasma and extravascular fluid until approximately half is partitioned in the extravascular space. Therefore a rapid initial drop in serum IgG is expected [ 11 ].

Studies show that the apparent half-life of Octagam 5% liquid is approximately 40 days in immunodeficient patients.

The main pharmacokinetic parameters of Octagam 5% liquid measured as total IgG in study OCTA-06 are displayed below:

In the pharmacokinetic study, a subset of 14 patients aged between 10 and 70 years with PI underwent pharmacokinetic assessments. Patients received infusions of Octagam 5% liquid (300 to 600 mg/kg) every 3 (n=6) to 4 (n=8) weeks for 12 months. Pharmacokinetic samples were collected at baseline and after the 5 th month of treatment. After the infusion, blood samples were taken until day 28 (for patients on a 21 day schedule, the interval was extended to 4 weeks for the pharmacokinetic study).

Table 9: PK Parameters of Octagam 5% liquid (Study OCTA-06)

 |  |  | Octagam | 5% liquid
 | N | Mean | SD | Median
Cmax (mg/mL) | 14 | 16.7 | 3.2 | 16.4
AUC (mg*h/mL) | 14 | 7022 | 1179 | 7103
T1/2 (days) | 14 | 40.7 | 17.0 | 36.3
Trough IgG Level; 21 Day Infusion Schedule (mg/dL) | 19 | 881.6 | 151.5 | 859
Trough IgG Level; 28 Day Infusion Schedule (mg/dL) | 25 | 763.5 | 156.8 | 760

The half-life of IgG can vary considerably from person to person. In particular, high concentrations of lgG and hypermetabolism associated with fever and infection have been seen to coincide with a shortened half-life of IgG. Longer half-lives are often seen with immunodeficient patients [ 12 ].

NON-CLINICAL TOXICOLOGY

Carcinogenesis, Mutagenesis, Impairment of Fertility

No studies were conducted on carcinogenesis, mutagenesis, or impairment of fertililty with Octagam 5% liquid.

Repeated-dose toxicity studies and the genotoxic studies gave no evidence of carcinogenic properties of TNBP and Octoxynol [ 13 ], [ 14 ].

The results of in vitro and in vivo genotoxicity studies for TNBP and Octoxynol were negative. The results of studies on the embryotoxic and teratogenic properties of TNBP and Octoxynol in rats and rabbits at a wide range of i.v. doses were also negative.

Animal Toxicology and/or Pharmacology

No studies were conducted on non-clinical pharmacology, toxicology, local tolerance or pharmacokinetics with Octagam 5% liquid.

A variety of single-dose toxicity studies were performed for TNBP and Octoxynol alone or in combination. The lowest toxic dose of TNBP + Octoxynol (1+5) was 10,000 mcg/kg BM in rats after intravenous administration. Studies on 13-week toxicity were performed for combinations of TNBP + Octoxynol in a broad dose range intravenously in dogs and rats. In these studies the lowest toxic dose for rats was local 60mcg TNBP/kg +300mcg Octoxynol/kg BM i.v. (concentration: 0.0006% and 0.003%, respectively) and systemic 300mcg TNBP/kg + 1,500mcg Octoxynol/kg BM i.v. (concentration: 0.003% and 0.015%, respectively). The lowest toxic dose for dogs was local 50 mcg TNBP/kg + 250mcg Octoxynol/kg BM i.v. (concentration: 0.005% and 0.025%, respectively) and systemic 500mcg TNBP/kg + 2,500mcg Octoxynol/kg BM i.v. (concentration: 0.05% and 0.25%, respectively).

Local tolerance of TNBP and Octoxynol was evaluated from the experiments on repeat-dose toxicity (rats, dogs) and on developmental toxicity (rats, rabbits). In these animal studies the lowest dose exerting local adverse reactions was 50 + 250 mcg/kg BM (TNBP + Octoxynol; daily injections) in dogs. At this dose 4 out of 6 dogs were affected starting in week 7 of treatment.

A pharmacokinetic study was carried out in rats given 300 mcg of TNBP/kg and 1,500 mcg Octoxynol/kg BM i.v. The plasma half-life for TNBP was approximately 20 minutes. Octoxynol was not detected.

CLINICAL STUDIES

In an open-label, multicenter study, 46 patients (including 10 patients between the ages of 6 and 12, and one 15 years old) with primary humoral immunodeficiency (PI) received Octagam 5% liquid individualized doses of 300 - 600 mg/kg every 3 or 4 weeks for 12 months. Six patients discontinued the study prematurely.

Eligible patients had to meet the following key inclusion criteria: aged 3 years or older; had a PI that had as a significant component hypogammaglobulinemia or antibody deficiency; had been receiving IGIV replacement therapy at a steady dose for at least 3 months prior to study entry and had maintained a trough level of at least 320 mg/dL above baseline serum IgG levels.

Patients were excluded if they had a history of severe reactions to blood or any blood-derived product; if they had a selective IgA deficiency or demonstrable antibodies to IgA; if they received blood or any blood product or derivative other than a commercially available IGIV within 3 months prior to study entry; if they had hepatic function abnormalities or a positive direct Coombs test at screening; if they had a pre-existing renal impairment, a history of drug or alcohol abuse in the previous 12 months or acquired medical condition known to cause secondary immune deficiency; if they were receiving long-term daily treatment with steroids at a dose of at least 1 mg/kg/day; if they had a requirement for pre-medication for IGIV infusion other than aspirin, acetaminophen, or other non-steroidal anti-inflammatory drug, or antihistamine; and if the received immunosuppressive or immunomodulatory drugs.

The primary efficacy endpoint was the number of episodes of serious infections/patient/year. Serious infection included pneumonia, bacteremia or sepsis, osteomyelitis/septic arthritis, visceral abscesses or bacterial or viral meningitis. Secondary efficacy variables were: the number of days of work/school missed; the number and days of hospitalizations; the number of visits to physicians for acute problems and/or visits to hospital emergency rooms; and the number of other infections documented by radiograph and fever.

For the primary endpoint, which was the number of episodes of serious infections, the observed rate was 0.1 infections per patient per year (5 infections over 43.5 patient-years).

Table 10: Summary of Secondary Efficacy Variables

Variable | Subjects N | Subjects % | Total Days or Visits | Total Subject Years | Days or Visits/Subj./YearEstimate
Work/School Days Missed | 30 | 65 | 241 | 43.5 | 5.5
Days in Hospital | 4 | 9 | 16 | 43.5 | 0.4
Visits to Physician/ER | 27 | 59 | 92 | 43.5 | 2.1

REFERENCES

1. Duhem, C., Dicato, M. A. and Ries, F. Side-effects of intravenous immune globulins. Clin. Exp. Immunol. 97 Suppl 1, 79-83 (1994).
2. Kannan, S., Rowland, C. H., Hockings, G. I. and Tauchmann, P. M. Intragam can interfere with blood glucose monitoring. Med. J. Aust. 180, 251-252 (2004).
3. Steinberger, B. A., Ford, S. M., Coleman, T. A. Intravenous Immunoglobulin Therapy Results in Post-infusional Hyperproteinemia, Increased Serum Viscosity, and Pseudohyponatremia. Am J Hematol 73:97-100 (2003)
4. Dalakas, M. C. High-dose intravenous immunoglobulin and serum viscosity: risk of precipitating thromboembolic events. Neurology 44, 223-226 (1994).
5. Wolberg, A. S., Kon, R. H., Monroe, D. M. and Hoffman, M. Coagulation factor XI is a contaminant in intravenous immunoglobulin preparations. Am. J Hematol. 65, 30-34 (2000).
6. Go RS, Call TG: Deep venous thrombosis of the arm after intravenous immunoglobulin infusion: case report and literature review of intravenous immunoglobulin-related thrombotic complications. Mayo Clin Proc75:83-85 (2000)
7. Sekul, E. A., Cupler, E. J. and Dalakas, M. C. Aseptic meningitis associated with high-dose intravenous immunoglobulin therapy: frequency and risk factors. Ann Intern. Med. 121, 259-262 (1994).
8. Pierce LR, Jain N: Risks associated with the use of intravenous immunoglobulin. Transfus Med Rev 17:241-251 (2003)
9. Kessary-Shoham H., Levy, Y., Shoenfeld, Y., Lorber, M. and Gershon, H. In vivo administration of intravenous immunoglobulin (IVIg) can lead to enhanced erythrocyte sequestration. Journal of Autoimmunity. 13, 129-135 (1999).
10. Rizk, A., Gorson, K. C., Kenney, L. and Weinstein, R. Transfusion-related acute lung injury after the infusion of IVIG. Transfusion 41, 264-268 (2001).
11. Koleba T, Ensom MH: Pharmacokinetics of intravenous immunoglobulin: a systematic review. Pharmacotherapy 26:813-827 (2006)
12. Lever, A. M., Yap, P. L., Cuthbertson, B., Wootton, R. and Webster, A. D. Increased half-life of gammaglobulin after prolonged intravenous replacement therapy. Clin Exp. Immunol 67, 441-446 (1987).
13. Auletta, CS., Kotkoskie, LA., Saulog, T., Richter, WR. A dietary oncogenicity study of tributyl phosphate in the CD-1 mouse. Toxicology 128, 135-141 (1998a).
14. Auletta CS., Weiner ML., Richter WR. A dietary toxicity/oncogenicity study of tributyl phosphate in the rat. Toxicology 128: 125-134 (1998b).

Octagam 5% liquid is supplied in 1.0 g, 2.5 g, 5 g, 10 g or 25 g single use bottles.

NDC Number | NDC Number | Size | Grams Protein
Octapharma Pharmazeutika Produktionsges.m.b.H | Octapharma AB
67467 – 843 - 01 | 68209 – 843 - 01 | 20 ml | 1.0
67467 – 843 – 02 | 68209 – 843 – 02 | 50 ml | 2.5
67467 – 843 – 03 | 68209 – 843 – 03 | 100 ml | 5.0
67467 – 843 – 04 | 68209 – 843 – 04 | 200 ml | 10.0
67467 – 843 – 05 |  | 500 ml | 25.0

Octagam 5% liquid is not supplied with an infusion set. If a filtered infusion set is used (not mandatory), the filter size must be 0.2 – 200 microns.

Components used in the packaging of Octagam 5% liquid are latex-free.

Octagam 5% liquid may be stored for 24 months at +2°C to + 25°C (36°F to 77°F) from the date of manufacture.

Do not use after expiration date.

Do not freeze. Frozen product should not be used.

Any unused product or waste material should be disposed of in accordance with local requirements.

PATIENT COUNSELING INFORMATION

Information for Patients

Inform patients of the early signs of hypersensitivity reactions including hives, generalised urticaria, tightness of the chest, wheezing, hypotension, and anaphylaxis. If allergic symptoms occur, patients should contact their physicians immediately.

Inform patients to also immediately report the following to their physician:

• signs and symptoms of renal failures, such as decreased urine output, sudden weight gain, fluid retention/edema, and/or shortness of breath

• signs and symptoms of aseptic meningitis, such as headache, neck stiffness, drowsiness, fever, sensitivity to light, painful eye movements, nausea, and vomiting

• signs and symptoms of hemolysis, such as fatigue, increased heart rate, yellowing of the skin or eyes, and dark-colored urine

• signs and symptoms of TRALI, such as severe respiratory distress, pulmonary edema, hypoxemia, normal left ventricular function, fever. TRALI typically occurs within 1 to 6 hours following transfusion

Inform patients that Octagam 5% liquid is made from human plasma and may contain infectious agents that can cause disease (e.g., viruses, and, theoretically, the CJD agent). Inform patients that the risk Octagam 5% liquid may transmit an infectious agent has been reduced by screening plasma donors for prior exposure to certain viruses, by testing the donated plasma for certain virus infections and by inactivating and/or removing certain viruses during manufacturing.

Inform patients that administration of IgG may interfere with the response to live viral vaccines such as measles, mumps and rubella. Inform patients to notify their immunizing physician of therapy with Octagam 5% liquid.

Octapharma USA Inc.Hoboken, NJ 07030

PACKAGE LABEL – PRINCIPAL DISPLAY PANEL

Immune Globulin Intravenous (Human), 5%

Octapharma Pharmazeutika Produktionsges.m.b.H

20 mL

NDC 67467-843-01

100mL

NDC 67467-843-03